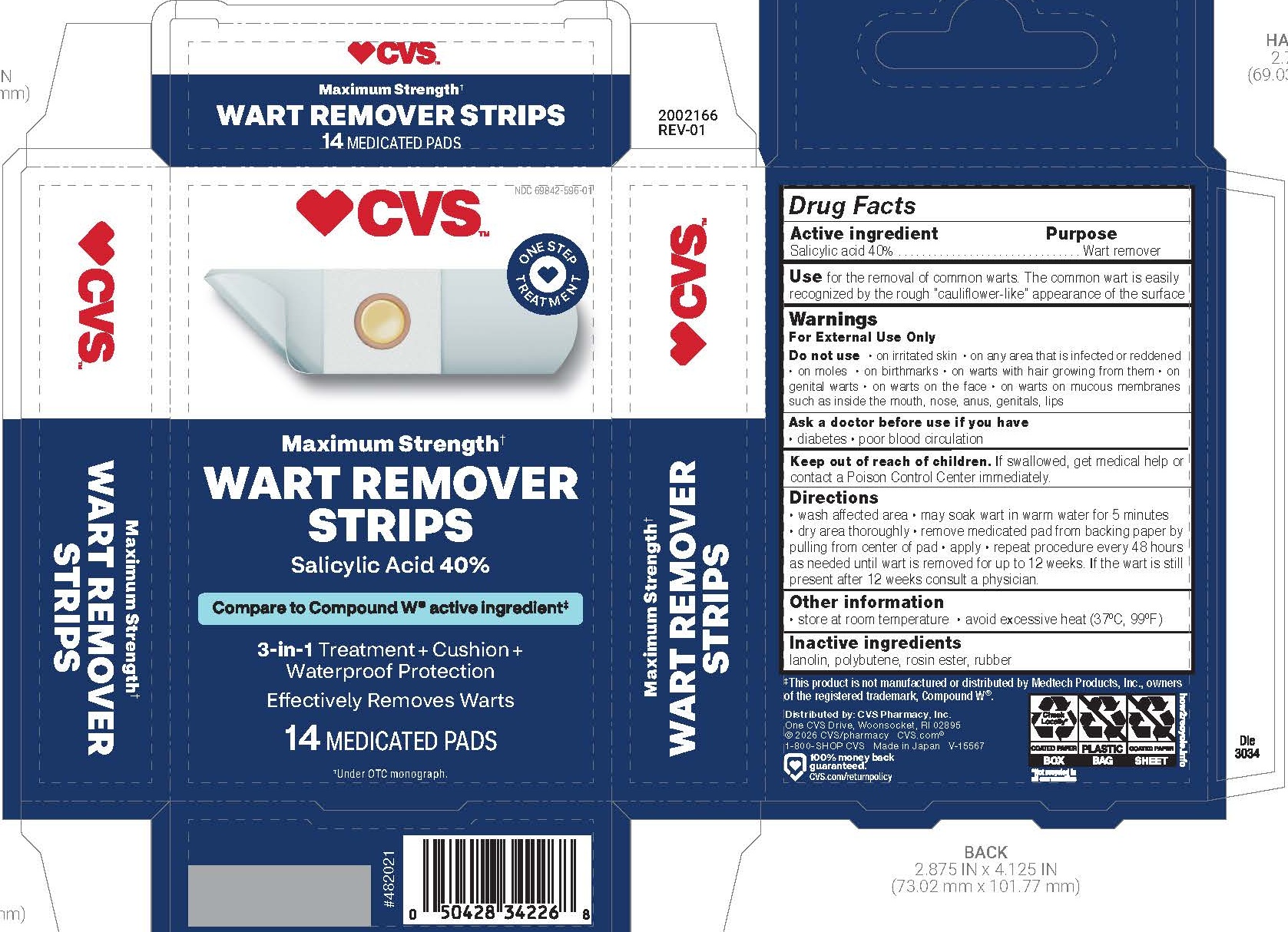 DRUG LABEL: SALICYLIC ACID WART REMOVER
NDC: 69842-596 | Form: STRIP
Manufacturer: CVS Pharmacy
Category: otc | Type: HUMAN OTC DRUG LABEL
Date: 20260127

ACTIVE INGREDIENTS: SALICYLIC ACID 40 mg/1 1
INACTIVE INGREDIENTS: POLYBUTENE (1400 MW); LANOLIN; NATURAL LATEX RUBBER

CVS Maximum Strength Wart Remover Strips

Active ingredient

Salicylic acid 40%

Purpose

Wart remover

Use

for the removal of common warts. The common wart is easily recognized by the rough "cauliflower-like" appearance of the surface

Warnings

For External Use Only

Do not use

- on irritated skin
- on any area that is infected or reddened
- on moles
- on birthmarks
- on warts with hair growing from them
- on genital warts
- on warts on the face
- on warts on mucous membranes such as inside the mouth, nose, anus, genitals, lips

Ask a doctor before use if you have

- diabetes
- poor blood circulation

Keep out of reach of children.

If swallowed, get medical help or contact a Poison Control Center immediately.

Directions

- wash affected area
- may soak wart in warm water for 5 minutes
- dry area thoroughly
- remove medicated pad from backing paper by pulling from center of pad
- apply
- repeat procedure every 48 hours as needed until wart is removed for up to 12 weeks. If the wart is still present after 12 weeks consult a physician.

Other information

- store at room temperature
- avoid excessive heat (37ºC, 99ºF)

Inactive ingredients

lanolin, polybutene, rosin ester, rubber

Principal Display Panel

CVS™

Maximum Strength+

Wart Remover Strips

Salicylic Acid 40%

Compare to Compound W active ingredient

3-in-1 Treatment+Cushion+Waterproof Protection

Efectively Removes Warts

14 MEDICATED PADS

+under OTC monograph